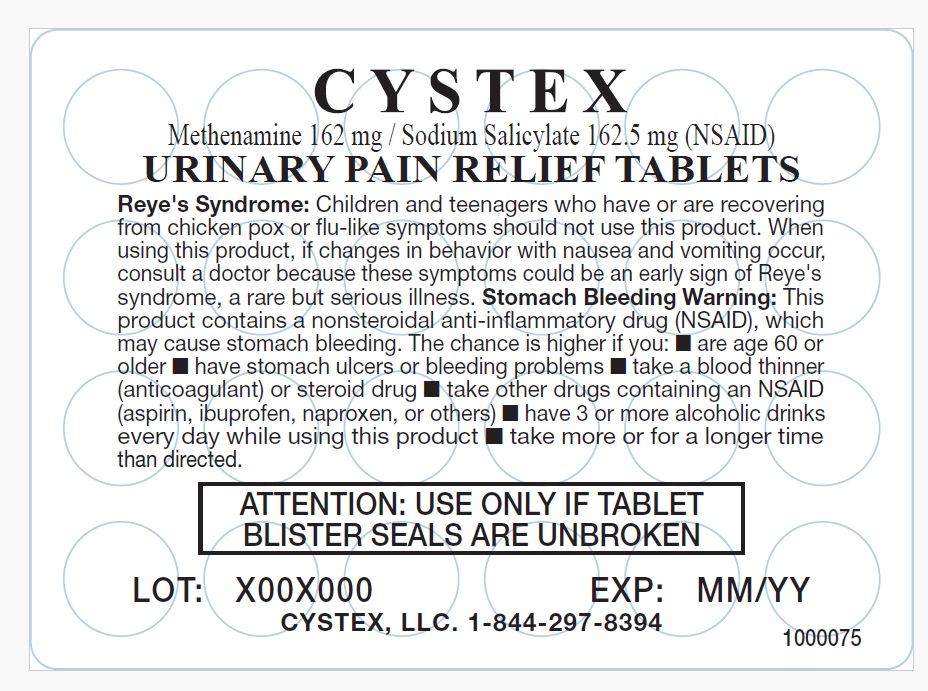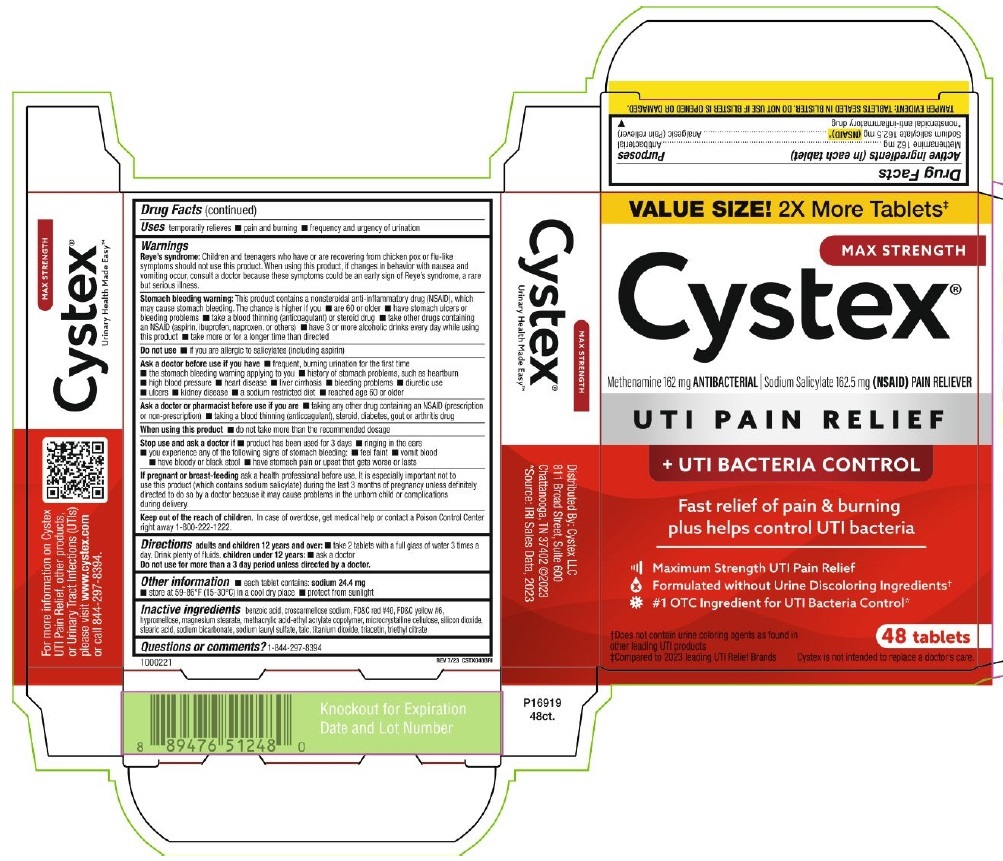 DRUG LABEL: Cystex 

NDC: 69693-512 | Form: TABLET
Manufacturer: Clarion Brands, LLC
Category: otc | Type: HUMAN OTC DRUG LABEL
Date: 20260114

ACTIVE INGREDIENTS: METHENAMINE 162 mg/1 1; SODIUM SALICYLATE 162.5 mg/1 1
INACTIVE INGREDIENTS: BENZOIC ACID; CROSCARMELLOSE SODIUM; FD&C RED NO. 40; FD&C YELLOW NO. 6; HYPROMELLOSE, UNSPECIFIED; MAGNESIUM STEARATE; METHACRYLIC ACID AND ETHYL ACRYLATE COPOLYMER; MICROCRYSTALLINE CELLULOSE; SILICON DIOXIDE; STEARIC ACID; SODIUM BICARBONATE; SODIUM LAURYL SULFATE; TALC; TITANIUM DIOXIDE; TRIACETIN; TRIETHYL CITRATE

Drug Facts

Active ingredients (in each tablet) | Purposes
Methenamine 162 mg | Antibacterial
Sodium Salicylate 162.5 mg (NSAID)* | Analgesic (Pain Reliever)
* nonsteroidal anti-inflammatory drug

INDICATIONS AND USAGE

Usestemporarily relieves

- pain & burning
- frequency and urgency of urination

Warnings

Reye's syndrome:Children and teenagers who have or are recovering from chicken pox or flu-like symptoms should not use this product. When using this product, if changes in behavior with nausea and vomiting occur, consult a doctor because these symptoms could be an early sign of Reye's syndrome, a rare but serious illness.

Stomach bleeding warning:This product contains a nonsteroidal anti-inflammatory drug (NSAID), which may cause stomach bleeding. The chance is higher if you

- are 60 or older
- have stomach ulcers or bleeding problems
- take a blood thinning (anticoagulant) or steroid drug
- take other drugs containing an NSAID (aspirin, ibuprofen, naproxen, or others)
- have 3 or more alcoholic drinks every day while using this product
- take more or for a longer time than directed

Do not use

- if you are allergic to salicylates (including aspirin)

Ask a doctor before use if you have

- frequent, burning urination for the first time
- the stomach bleeding warning applying to you
- history of stomach problems, such as heartburn
- high blood pressure
- heart disease
- liver cirrhosis
- bleeding problems
- diuretic use
- ulcers
- kidney disease
- a sodium restricted diet
- reach age 60 or older

Ask a doctor or pharmacist before use if you are

- taking any other drug containing an NSAID (prescription or non-prescription)
- taking a blood thinning (anticoagulant), steroid, diabetes, gout or arthritis drug

When using this product

- do not take more than the recommended dosage

Stop use and ask a doctor if

- product has been used for 3 days
- ringing in the ears
- you experience any of the following signs of stomach bleeding:
  - feel faint
  - vomit blood
  - have bloody or black stools
  - have stomach pain or upset that gets worse or lasts

PREGNANCY OR BREAST FEEDING

If pregnant or breast feeding ask a health professional before use. It is especially important not to use this product (which contains sodium salicylate) during the last 3 months of pregnancy unless definitely directed to do so by a doctor because it may cause problems in the unborn child or complications during delivery.

KEEP OUT OF REACH OF CHILDREN

Keep out of the reach of children.In case of overdose, get medical help or contact a Poison Control Center right away 1-800-222-1222.

Directions

Adults and children 12 years and over:

- take 2 tablets with a full glass of water 3 times a day. Drink plenty of fluids.

Children under 12 years:

- ask a doctor.

Do not use for more than a 3 day period unless directed by a doctor.

Other information

- each tablet contains:sodium 24.4 mg
- store at 59-86°F (15-30°C) in a cool dry place
- protect from sunlight

Inactive ingredients

benzoic acid, croscarmellose sodium, fd&c red #40, fd&c yellow #6, hypromellose , magnesium stearate, methacrylic acid-ethyl acrylate copolymer, microcrystalline cellulose, silicon dioxide, stearic acid, sodium bicarbonate, sodium lauryl sulfate, talc, titanium dioxide, triacetin, triethyl titanium dioxide, triethyl citrate

Questions or comments?

1-844-297-8394

PRINCIPAL DISPLAY PANEL

VALUE SIZE!2x More Tablets‡
MAX STRENGTH
Cystex®
Methenamine 162 mg ANTIBACTERIAL ∣ Sodium Salicylate 162.5 mg (NSAID) PAIN RELIEVER
UTI PAIN RELIEF
+ UTI BACTERIA CONTROL
Fast relief of pain & burning
plus helps control UTI bacteria
Maximum Strength UTI Pain Relief
Formulated without Urine Discoloring Ingredients†
#1 OTC Ingredient for UTI Bacteria Control*
†Does not contain urine coloring agents as found in
other leading UTI products
‡Compared to 2023 leading UTI Relief Brands
48 Tablets
Cystex is not intended to replace a doctor's care.
TAMPER EVIDENT: TABLETS SEALED IN BLISTER. DO NOT USE IF BLISTER IS OPENED OR DAMAGED.
1000221
REV 7/23 CSTX048BRI
MAX STRENGTH
Cystex®
Urinary Health Made Easy™
For more information on Cystex
UTI Pain Relief, other products,
or Urinary Tract Infections (UTIs)
please visit www.cyxtex.com
or call 844-297-8394
MAX STRENGTH
Cystex®
Urinary Health Made Easy™
Distributed by: Cystex, LLC
811 Broad Street, Suite 600
Chattanooga, TN 37402 @2023
*Source: IRI Sales Data, 2023
P16919
48ct.
Knockout for Expiration
Date and Lot Number

Principal Display for Blister Pack

CYSTEX
Methenamine 162 mg / Sodium Salicylate 162.5 mg (NSAID)
URINARY PAIN RELIEF TABLETS
Reye's Syndrome:Children and teenagers who have or are recovering
from chicken pox or flu-like symptoms should not use this product. When
using this product, if changes in behavior with nausea and vomiting occur,
consult a doctor because these symptoms could be an early sign of Reye's
syndrome, a rare but serious illness. Stomach Bleeding Warning:This
product contains a nonsteroidal anti-inflammatory drug (NSAID), which
may cause stomach bleeding. The chance is higher if you: ■ are age 60 or
older ■ have stomach ulcers or bleeding problems ■ take a blood thinner
(anticoagulant) or steroid drug ■ take other drugs containing an NSAID
(aspirin, ibuprofen, naproxen, or others) ■ have 3 or more alcoholic drinks
every day while using this product ■ take more or for a longer time
than directed.
ATTENTION: USE ONLY IF TABLET
BLISTER SEALS ARE UNBROKEN
LOT: X00X000 EXP: MM/YY
CYSTEX, LLC. 1-844-297-8394
1000075